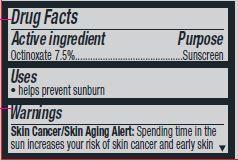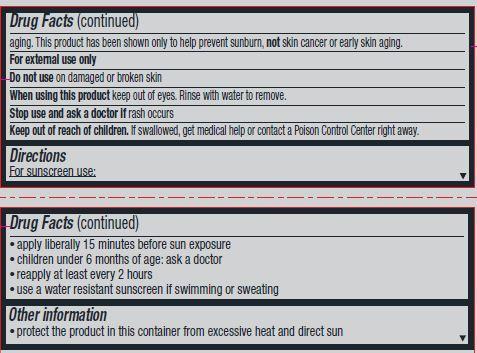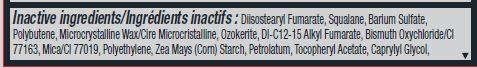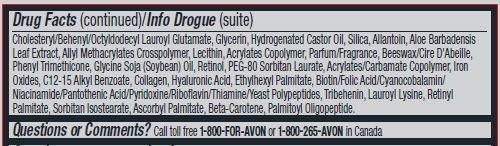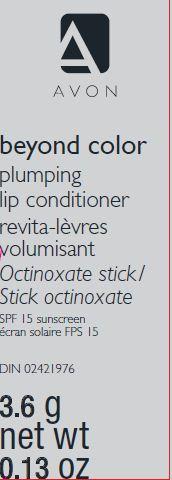 DRUG LABEL: Beyond Color
NDC: 10096-0321 | Form: LIPSTICK
Manufacturer: Avon Products, Inc
Category: otc | Type: HUMAN OTC DRUG LABEL
Date: 20140926

ACTIVE INGREDIENTS: OCTINOXATE 75 mg/1 g

Active ingredient
Octinoxate 7.5%................................

Purpose
...............................Sunscreen

Uses
• helps prevent sunburn

Warnings
Skin Cancer/Skin Aging Alert: Spending time in the sun increases your risk of skin cancer and early skin aging. This product has been shown only to help prevent sunburn, not skin cancer or early skin aging.
For external use only

Do not use on damaged or broken skin

When using this product keep out of eyes. Rinse with water to remove.

Stop use and ask a doctor if rash occurs

Keep out of reach of children. If swallowed, get medical help or contact a poison control center right away.

Directions

For sunscreen use:
• apply liberally 15 minutes before sun exposure
• children under 6 months of age: ask a doctor
• reapply at least every 2 hours
• use a water resistant sunscreen if swimming or sweating

Other information
• protect the product in this container from excessive heat and direct sun

INACTIVE INGREDIENT

Inactive ingredients:Diisostearyl Fumarate, Squalane, Barium Sulfate, Polybutene, Microcrystalline Wax/Cire Microcristalline, Ozokerite, DI-C12-15 Alkyl Fumarate, Bismuth Oxychloride/CI 77163, Mica/CI 77019, Polyethylene, Zea Mays (Corn) Starch, Petrolatum, Tocopheryl Acetate, Caprylyl Glycol, Cholesteryl/Behenyl/Octyldodecyl Lauroyl Glutamate, Glycerin, Hydrogenated Castor Oil, Silica, Allantoin, Aloe Barbadensis Leaf Extract, Allyl Methacrylates Crosspolymer, Lecithin, Acrylates Copolymer, Parfum/Fragrance, Beeswax/Cire D'Abeille,
Phenyl Trimethicone, Glycine Soja (Soybean) Oil, Retinol, PEG-80 Sorbitan Laurate, Acrylates/Carbamate Copolymer, Iron Oxides, C12-15 Alkyl Benzoate, Collagen, Hyaluronic Acid, Ethylhexyl Palmitate, Biotin/Folic Acid/Cyanocobalamin/Niacinamide/Pantothenic Acid/Pyridoxine/Riboflavin/Thiamine/Yeast Polypeptides, Tribehenin, Lauroyl Lysine, Retinyl Palmitate, Sorbitan Isostearate, Ascorbyl Palmitate, Beta-Carotene, Palmitoyl Oligopeptide.

Questions or Comments?
Call toll free 1-800-FOR-AVON or 1-800-265-AVON in Canada